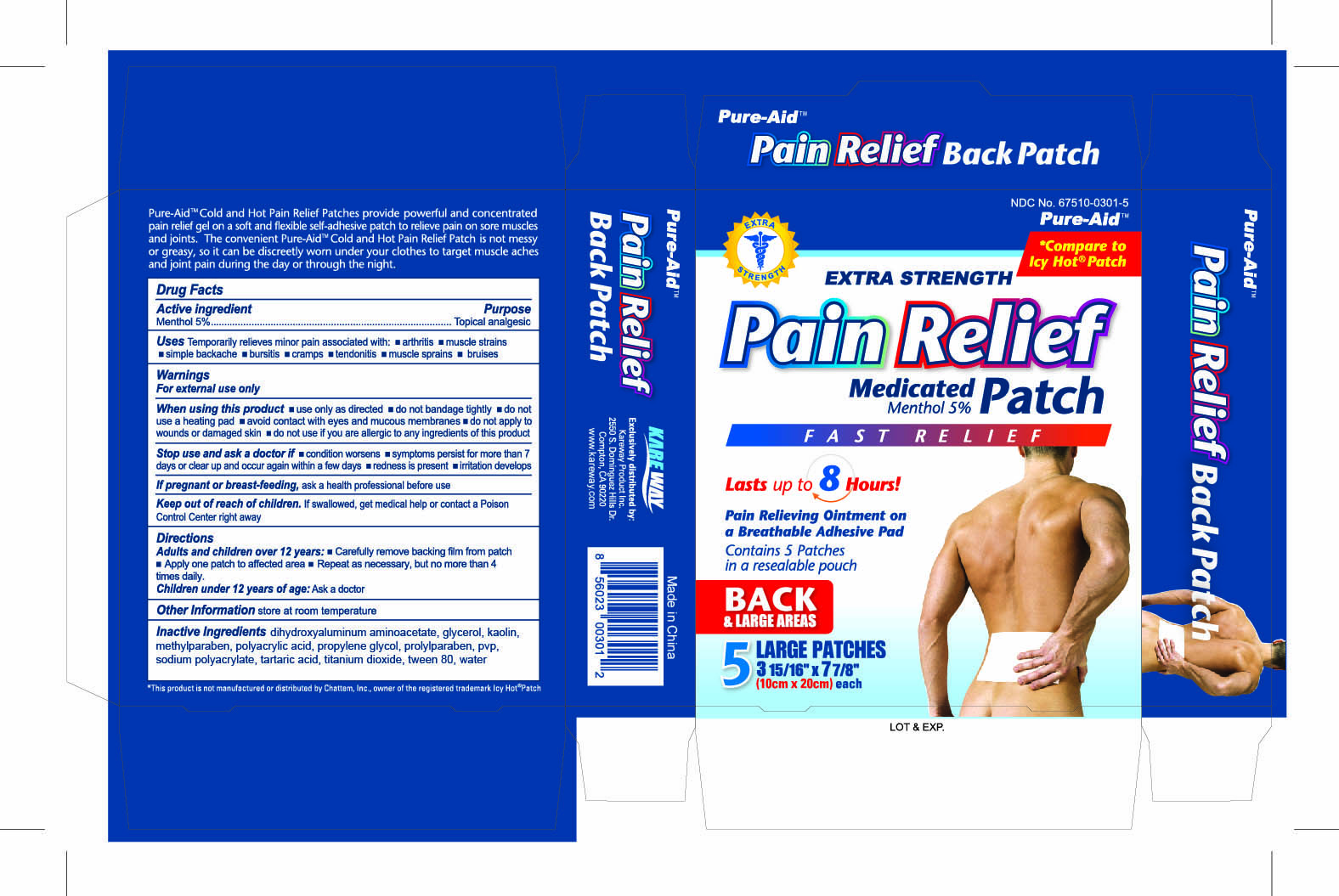 DRUG LABEL: Medicated Pain Relief
NDC: 67510-1301 | Form: PATCH
Manufacturer: Kareway Product, Inc.
Category: otc | Type: HUMAN OTC DRUG LABEL
Date: 20190307

ACTIVE INGREDIENTS: MENTHOL 400 mg/1 1
INACTIVE INGREDIENTS: WATER; SODIUM POLYACRYLATE (8000 MW); DIHYDROXYALUMINUM AMINOACETATE; KAOLIN; GLYCERIN; POVIDONE; METHYLPARABEN; POLYETHYLENE GLYCOL 400; POLYSORBATE 80; PROPYLPARABEN; POLYACRYLIC ACID (8000 MW); TARTARIC ACID; TITANIUM DIOXIDE

Drug Facts

Active Ingredient

L-Menthol 5%

Purpose

Topical analgesic

Uses

Temporarily relieves minor pain associated with:

- arthritis
- simple backache
- bursitis
- muscle sprains
- bruises

Warnings

For external use only

When using this product

- use only as directed
- do not bandage tightly or use a heating pad
- avoid contact with eyes and mucous membrane
- do not apply to wounds or damaged skin

Stop use and ask a doctor if

- condition worsens
- symptoms persist for more than 7 days or clear up and occur again within a few days
- redness is present
- irritation develops

If pregnant or breast-feeding,

ask a health professional before use.

Keep out of reach of children.

If swallowed, get medical help or contact a Poison Control Center right away.

Directions

Adults and children over 12 years:

- Carefully remove backing film from patch
- Apply one patch to affected area
- Repeat as necessary, but no more than 4 times daily.

Children 12 years or younger:

ask a doctor

Other Information

store at room temperature

Inactive ingredients

dihydroxyaluminum aminoacetate, glycerol, kaolin, methylparaben, polyacrylic acid, propylene glycol, propylparaben, pvp, sodium polyacrylate, tartaric acid, titanium dioxide, tween 80, water

package label

Pain Relief Medicated Patch